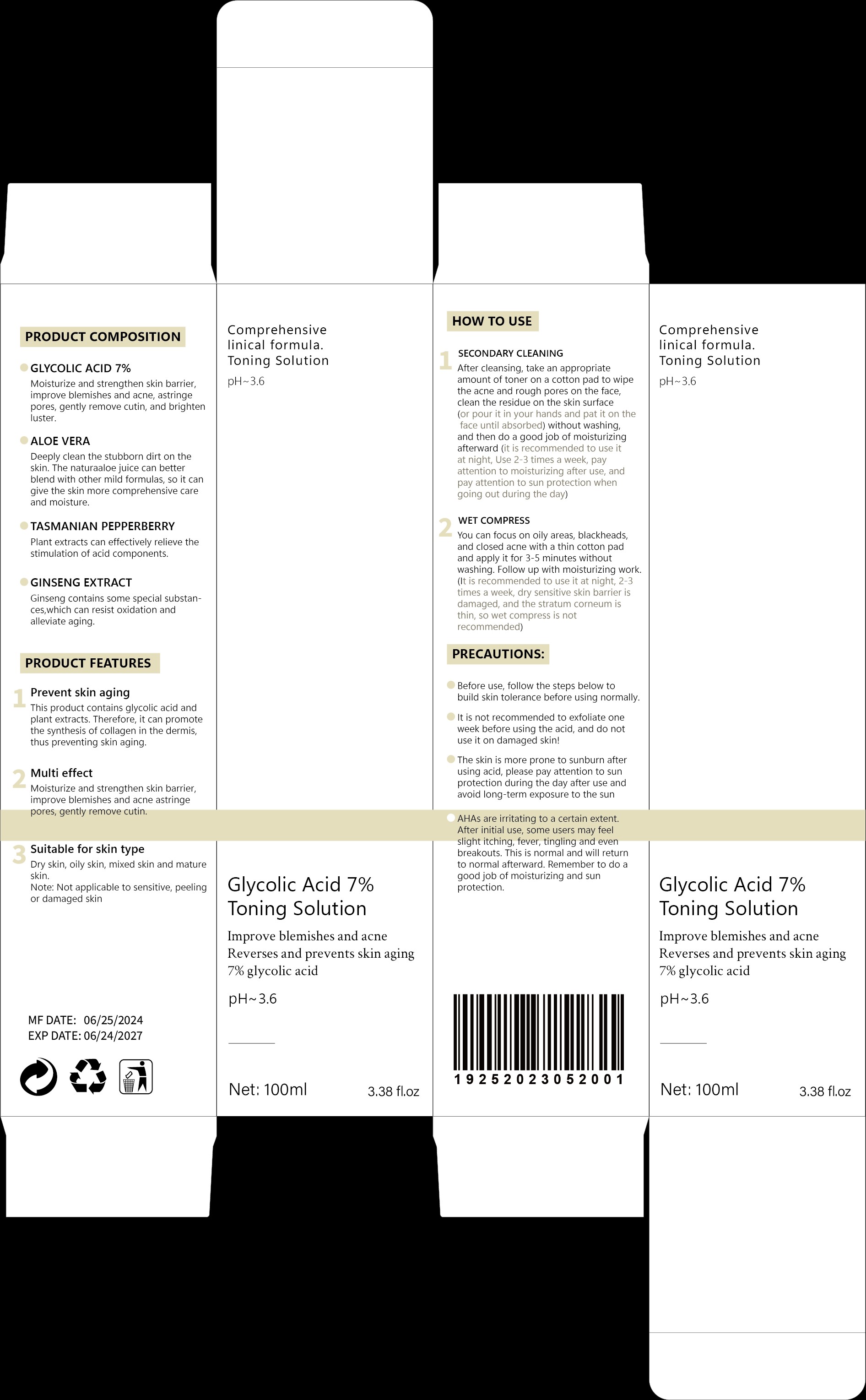 DRUG LABEL: Glycolic Acid 7% Toning Solution
NDC: 84732-001 | Form: LIQUID
Manufacturer: Dongguan Haiyi Technology Co., Ltd.
Category: otc | Type: HUMAN OTC DRUG LABEL
Date: 20240913

ACTIVE INGREDIENTS: GLYCOLIC ACID 7 mg/100 mL
INACTIVE INGREDIENTS: ALOE VERA LEAF; AMERICAN GINSENG; TASMANNIA LANCEOLATA WHOLE

Active ingredient

GLYCOLIC ACID 7%

Inactive ingredient

ALOE VERA

TASMANIAN PEPPERBERRY
GINSENG EXTRACT

Purpose section

Improve blemishes and acneReverses and prevents skin aging7% glycolic acid

Warning

Before use, follow the steps below tobuild skin tolerance before using normally.
It is not recommended to exfoliate oneweek before using the acid, and do notuse it on damaged skin!
The skin is more prone to sunburn afterusing acid, please pay attention to sunprotection during the day after use andavoid long-term exposure to the sun
AHAs are irritating to a certain extent.After initial use, some users may feelslight itching, fever, tingling and evenbreakouts. This is normal and will returnto normal afterward. Remember to do agood job of moisturizing and sunprotection.

stop use

if have the severe allergic reaction stop to use

not use

Pregnant women or severe skin diseases not to use

OUT OF CHILDREN

KEEP THE PRODUCT OUT OF REACH OF CHILDREN to

HOW TO USE

SECONDARY CLEANING
After cleansing, take an appropriateamount of toner on a cotton pad to wipethe acne and rough pores on the faceclean the residue on the skin surface(or pour it in your hands and pat it on theface until absorbed) without washing,and then do a good job of moisturizingafterward (it is recommended to use itat night, Use 2-3 times a week, payattention to moisturizing after use, andpay attention to sun protection whengoing out during the day)
WET COMPRESS
You can focus on oily areas, blackheadsand closed acne with a thin cotton padand apply it for 3-5 minutes withoutwashing.Follow up with moisturizing work(lt is recommended to use it at night,2-3times a week, dry sensitive skin barrier isdamaged, and the stratum corneum isthin, so wet compress is notrecommended)

Dosage

take an appropriateamount,Use 2-3 times a week

PACKAGE LABEL

PRODUCT COMPOSITION
GLYCOLIC ACID 7%
Moisturize and strengthen skin barrierimprove blemishes and acne, astringepores,gently remove cutin,and brightenluster.
ALOE VERA
Deeply clean the stubborn dirt on theskin.The naturaaloe juice can betterblend with other mild formulas, so it cangive the skin more comprehensive careand moisture.
TASMANIAN PEPPERBERRY
Plant extracts can effectively relieve thestimulation of acid components.
GINSENG EXTRACT
Ginseng contains some special substances,which can resist oxidation andalleviate aging.
PRODUCT FEATURES
Prevent skin aging
This product contains glycolic acid andplant extracts.Therefore,it can promotethe synthesis of collagen in the dermis,thus preventing skin aging.
Multi effectMoisturize and strengthen skin barrierimprove blemishes and acne astringepores,gently remove cutin.